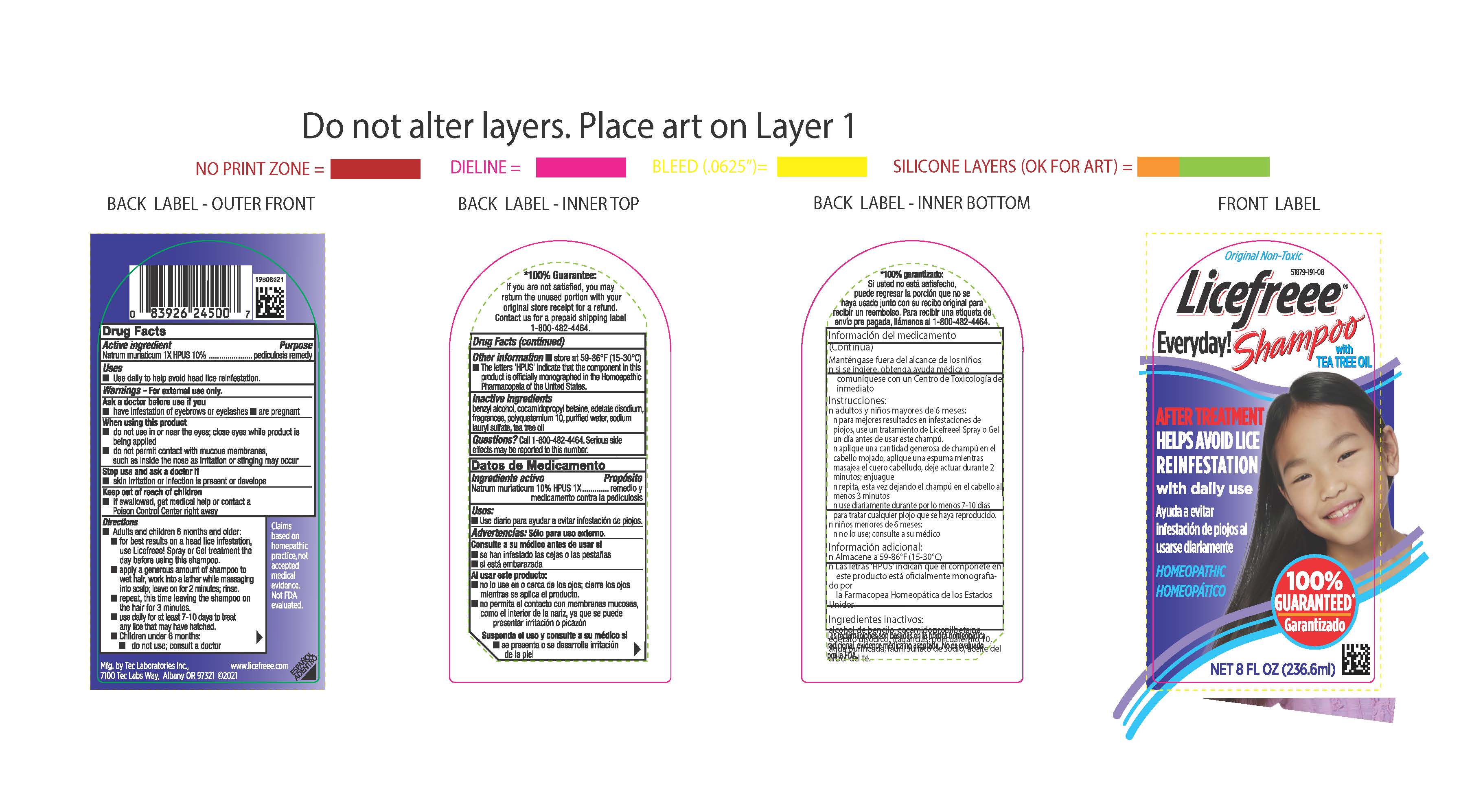 DRUG LABEL: Licefreee Everyday
NDC: 51879-191 | Form: SHAMPOO
Manufacturer: Tec Laboratories,Inc.
Category: homeopathic | Type: HUMAN OTC DRUG LABEL
Date: 20241105

ACTIVE INGREDIENTS: SODIUM CHLORIDE 1 [hp_X]/1 mL
INACTIVE INGREDIENTS: EDETATE DISODIUM; BENZYL ALCOHOL; WATER; SODIUM LAURYL SULFATE; TEA TREE OIL; COCAMIDOPROPYL BETAINE; POLYQUATERNIUM-10 (125 MPA.S AT 2%)

LiceFreee Everyday Shampoo

Active ingredient

Natrum munaticum 1X HPUS (Sodium chloride)

Purpose

pediculosis remedy

Uses

Use daily to help aviod had lice reinfestation.

Warnings

For external use only

Ask a doctor before use if you have

- have infestation of eyebrows or eyelashes
- are pregnant

When using this product

•do not use in or near the eyes;close eyes while product is being applied

•do not permit contact with mucous membranes, such as inside the nose,as irritation or stinging may occur

Stop use and ask a doctor if

•skin irritation or infection is present or develops

Keep out of reach of children

- if swallowed, get medical help or contact a Poison Control Center right away.

Other information

store at 59-86ºF (15-30ºC)

Directions

- adults and children 6 months of age and older:
- for best results on a head lice infestation,use Licefreee! Spray or Gel treatment the day before using this shampoo.
- apply a generous amount of shampoo to wet hair,work into a lather while massaging into scalp;rinse.
- repeat, this time leaving the shampoo on the hair for 3 minutes; rinse
- use daily for at least 7-10 days to treat any lice that may have hatched.

Inactive ingredients

benzyl alcohol, cocamidopropyl betaine, disodium EDTA,

fragrances, polyquarernium 10, purified water, soldium lauryl sulfate, tea tree oil

Questions?

Call 1-800-482-4464. Serious side effects may be reported to this number

RECENT MAJOR CHANGES

- repeat, this time leaving the shampoo on the hair for 3 minutes

PACKAGE LABEL

Original Non-Toxic

Licefreee

Everyday!Shampoo

with

TEA TREE OIl

HELPS AVOID LICE REINFESTATION

with daily use

Ayuda a evitar

infestacion de piojos al

usarse diariamente

HOMEOPATHIC

8 FL OZ (236.6ml)